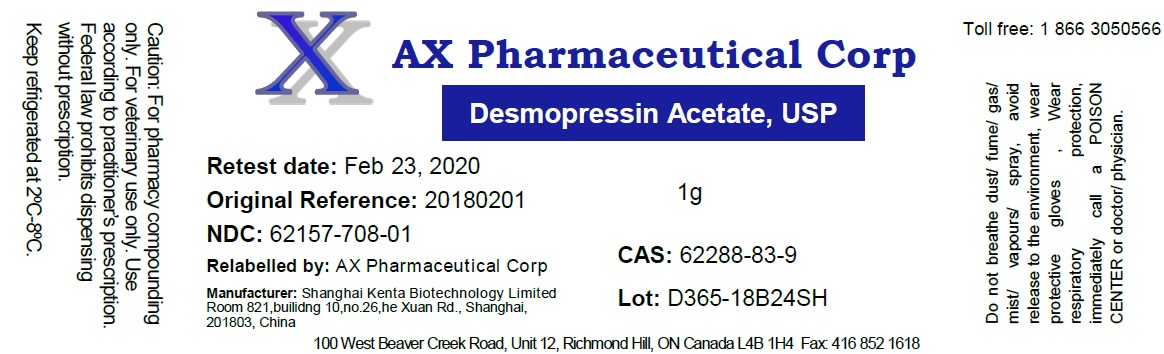 DRUG LABEL: Desmopressin Acetate
NDC: 62157-708 | Form: POWDER
Manufacturer: AX Pharmaceutical Corp
Category: other | Type: BULK INGREDIENT
Date: 20181030

ACTIVE INGREDIENTS: DESMOPRESSIN ACETATE 0.99 g/1 g
INACTIVE INGREDIENTS: WATER

Desmopressin Acetate